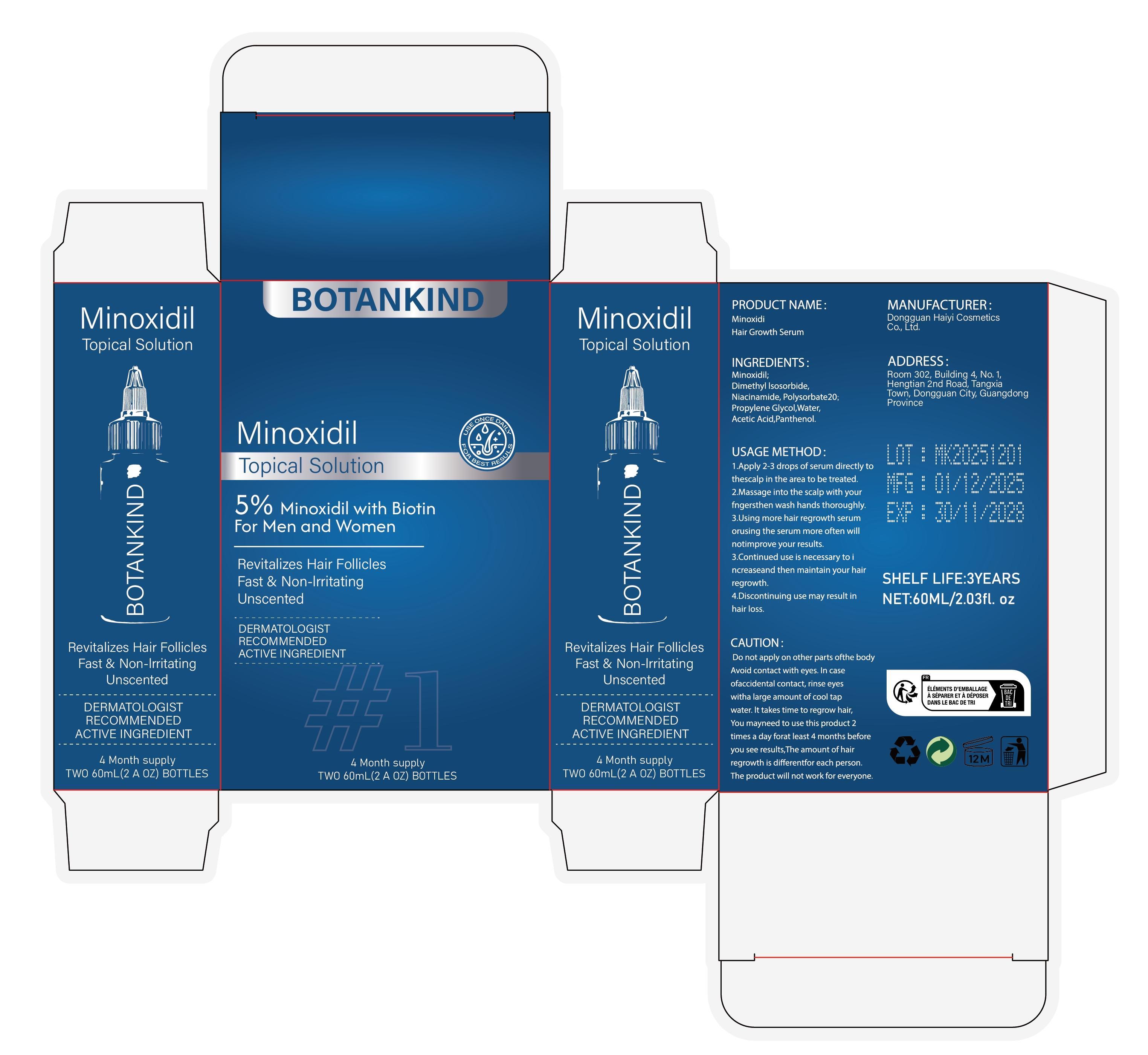 DRUG LABEL: Minoxidi Hair Growth Serum
NDC: 85594-010 | Form: LIQUID
Manufacturer: Dongguan Haiyi Cosmetics Co., Ltd.
Category: otc | Type: HUMAN OTC DRUG LABEL
Date: 20251210

ACTIVE INGREDIENTS: MINOXIDIL 5 mg/120 mL
INACTIVE INGREDIENTS: ACETIC ACID; NIACINAMIDE; WATER; POLYSORBATE 20; DIMETHYL ISOSORBIDE; PROPYLENE GLYCOL; PANTHENOL

85594-010-01 Minoxidi Hair Growth Serum

ACTIVE INGREDIENT

Minoxidil

INACTIVE INGREDIENT

Dimethyl lsosorbide,Niacinamide, Polysorbate20，Propylene Glycol,Water,Acetic Acid,Panthenol.

PURPOSE

Revitalizes Hair Follicles Fast & Non-lrritating Unscented

WARNINGS

Do not apply on other parts ofthe body Avoid contact with eyes. In case of accidental contact, rinse eyes with a large amount of cool tap water. lt takes time to regrow hair,You may need to use this product 2 times a day forat least 4 months before you see results,The amount of hair regrowth is different for each person.The product will not work for everyone.

STOP USE

lf you experience any discomfort,please stop using it immediately.

DO NOT USE

Not suitable for use by children, pregnantor breast feeding people.

KEEP OUT OF REACH OF CHILDREN

KEEP THE PRODUCT OUT OF REACH OF CHILDREN to

INDICATIONS AND USAGE

1.Apply 2-3 drops of serum directly tthescalp in the area to be treated.

2.Massage into the scalp with yourfngersthen wash hands thoroughly.

3.Using more hair regrowth serumorusing the serum more often willnotimprove your results.

4.Continued use is necessary to increaseand then maintain your hairregrowth.

5.Discontinuing use may result in
hair loss.

DOSAGE AND ADMINISTRATION

Apply 2-3 drops of serum directly to the scalp in the area to be treated